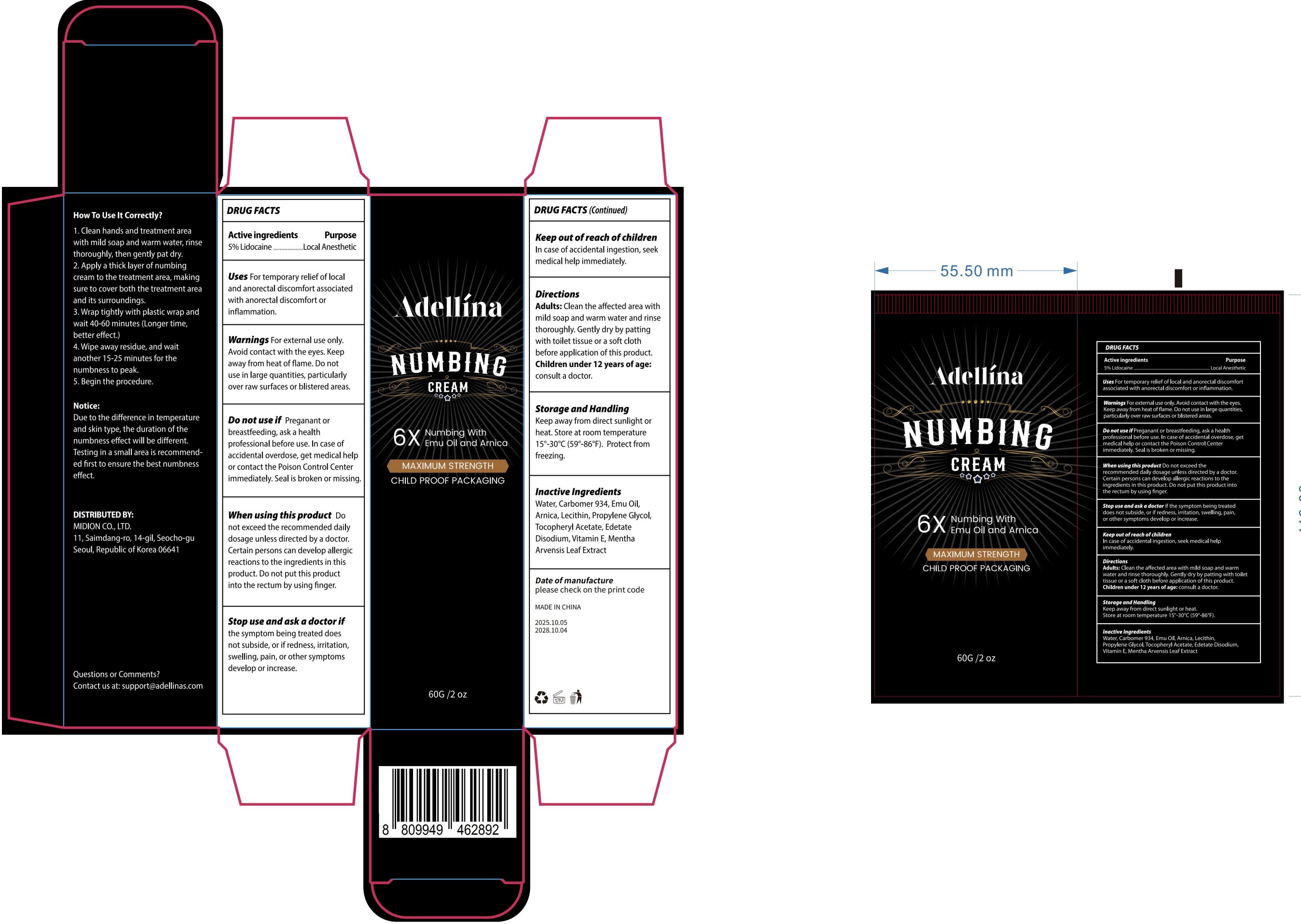 DRUG LABEL: Adellina Lidocaine Numbing Cream Anorectal(Hemorrhoidal) Cream
NDC: 60771-0041 | Form: CREAM
Manufacturer: Guangzhou Haishi Biological Technology Co., Ltd.
Category: otc | Type: HUMAN OTC DRUG LABEL
Date: 20251021

ACTIVE INGREDIENTS: LIDOCAINE 5 g/100 g
INACTIVE INGREDIENTS: PORTULACA OLERACEA WHOLE; GLYCERIN; EDETATE DISODIUM; 1,2-HEXANEDIOL; CHRYSANTHELLUM INDICUM WHOLE; AQUA; MENTHA ARVENSIS LEAF; PROPYLENE; CARBOMER; HYDROXYACETOPHENONE; PEG-40 HYDROGENATED CASTOR OIL

Adellina Lidocaine Numbing Cream Anorectal(Hemorrhoidal) Cream

Active Ingredients

Lidocaine 5%

Purpose

For temporary relief of localand anorectal discomfort associatedwith anorectal discomfort orinflammation.

Uses

1.Clean hands and treatment areawith mild soap and warm water, rinsethoroughly, then gently pat dry.
2. Apply a thick layer ofnumbingcream to the treatment area, makingsure to cover both the treatment areaand its surroundings.
3. Wrap tightly with plastic wrap andwait 40-60 minutes (Longer time,better effect.)
4. Wipe away residue, and waitanother 15-25 minutes for thenumbness to peak.
5. Begin the procedure.

Warnings

For external use only. Avoid contact with the eyes Keep away from heat or flame. Do not use in large quantities, particularly over raw surfaces or blistered areas.

Stop Use

Stop use and ask a doctor if redness, irritation, swelling, pain, or other symptoms occurs,or If condition worsens, or if symptoms persist for more than 7 days or clear up and occur again within a few days.

Do not use this product if Pregnant or breastfeeding, ask a health professional before use. In case of accidental overdose, get medical help or contact the Poison Control Center immediately. Seal is broken or missing.

When Using

Do not exceed the recommended daily dosage unless directed by a doctor. certain persons can develop allergic reactions to ingredients in this product. do not put this product into the rectum by using finger.

Keep Out Of Reach Of Children

In case of accidental ingestion, seek medical help immediately.

Dosage & administration

Apply an appropriate amount of ointment evenly to the affected area，do not use in large quantities

Inactive ingredients

AQUA 71.3%
PROPYLENE 5%
CARBOMER 0.25%
GLYCERIN 5%
DISODIUM EDTA 0.05%
HYDROXYACETOPHENONE 0.4%
1,2-HEXANEDIOL 5%
MENTHA ARVENSIS LEAF EXTRACT 2%
CHRYSANTHELLUM INDICUM EXTRACT 2%

PORTULACA OLERACEA EXTRACT 2%

PEG-40 HYDROGENATED CASTOR OIL 2%